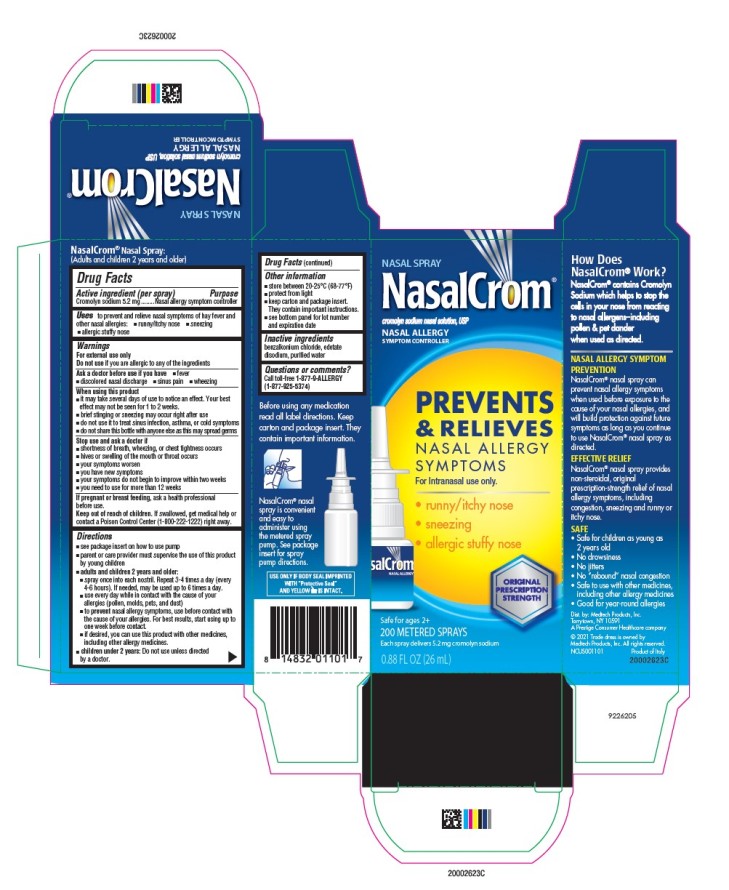 DRUG LABEL: NasalCrom
NDC: 52183-199 | Form: SPRAY, METERED
Manufacturer: Prestige Brands Holdings, Inc.
Category: otc | Type: HUMAN OTC DRUG LABEL
Date: 20251030

ACTIVE INGREDIENTS: CROMOLYN SODIUM 5.2 mg/1 1
INACTIVE INGREDIENTS: BENZALKONIUM CHLORIDE; EDETATE DISODIUM; WATER

NasalCrom

NasalCrom

Drug Facts

Active ingredient (per spray)

Cromolyn sodium 5.2mg

Purpose

Nasal allergy symptom controller

Uses

to prevent and relieve nasal symptoms of hay fever and other nasal allergies:

- runny/itchy nose
- sneezing
- allergic stuffy nose

Warnings

For external use only

Do not use

if you are allergic to any of the ingredients

Ask a doctor before use if you have

- fever
- discolored nasal discharge
- sinus pain
- wheezing

When using this product

- it may take several days of use to notice an effect. Your best effect may not be seen for 1 to 2 weeks.
- brief stinging or sneezing may occur right after use
- do not use it to treat sinus infection, asthma, or cold symptoms
- do not share this bottle with anyone else as this may spread germs

Stop use and ask a doctor if

- shortness of breath, wheezing, or chest tightness occurs
- hives or swelling of the mouth or throat occurs
- your symptoms worsen
- you have new symptoms
- your symptoms do not begin to improve within two weeks
- you need to use for more than 12 weeks

If pregnant or breast-feeding,

ask a health professional before use.

Keep out of reach of children.

If swallowed, get medical help or contact a Poison Control Center (1-800-222-1222) right away.

Directions

- see package insert on how to use pump
- parent or care provider must supervise the use of this product by young children
- adults and children 2 years and older:
- spray once into each nostril. Repeat 3-4 times a day (every 4-6 hours). If needed, may be used up to 6 times a day.
- use every day while in contact with the cause of your allergies (pollen, molds, pets, and dust)
- to prevent nasal allergy symptoms, use before contact with the cause of your allergies. For best results, start using up to one week before contact.
- if desired, you can use this product with other medicines, including other allergy medicines.
- children under 2 years: Do not use unless directed by a doctor.

Other information

- store between 20°-25°C (68°-77°F)
- protect from light
- keep carton and package insert. They contain important instructions.
- see bottom panel for lot number and expiration date

Inactive ingredients

benzalkonium chloride, edetate disodium, purified water

Questions or comments?

call 1-877-9-ALLERGY (1-877-925-5374)

Principal Display Panel

NASAL SPRAY

NasalCrom ®

cromolyn sodium nasal solution, USP
NASAL ALLERGY SYMPTOM CONTROLLER

Original Prescription Strength

Safe for ages 2+

100 Metered Sprays / Each spray delivers 5.2 mg cromolyn sodium

0.44 FL OZ (13 mL)

200 Metered Sprays / Each spray delivers 5.2 mg cromolyn sodium

0.88 FL OZ (26 mL)